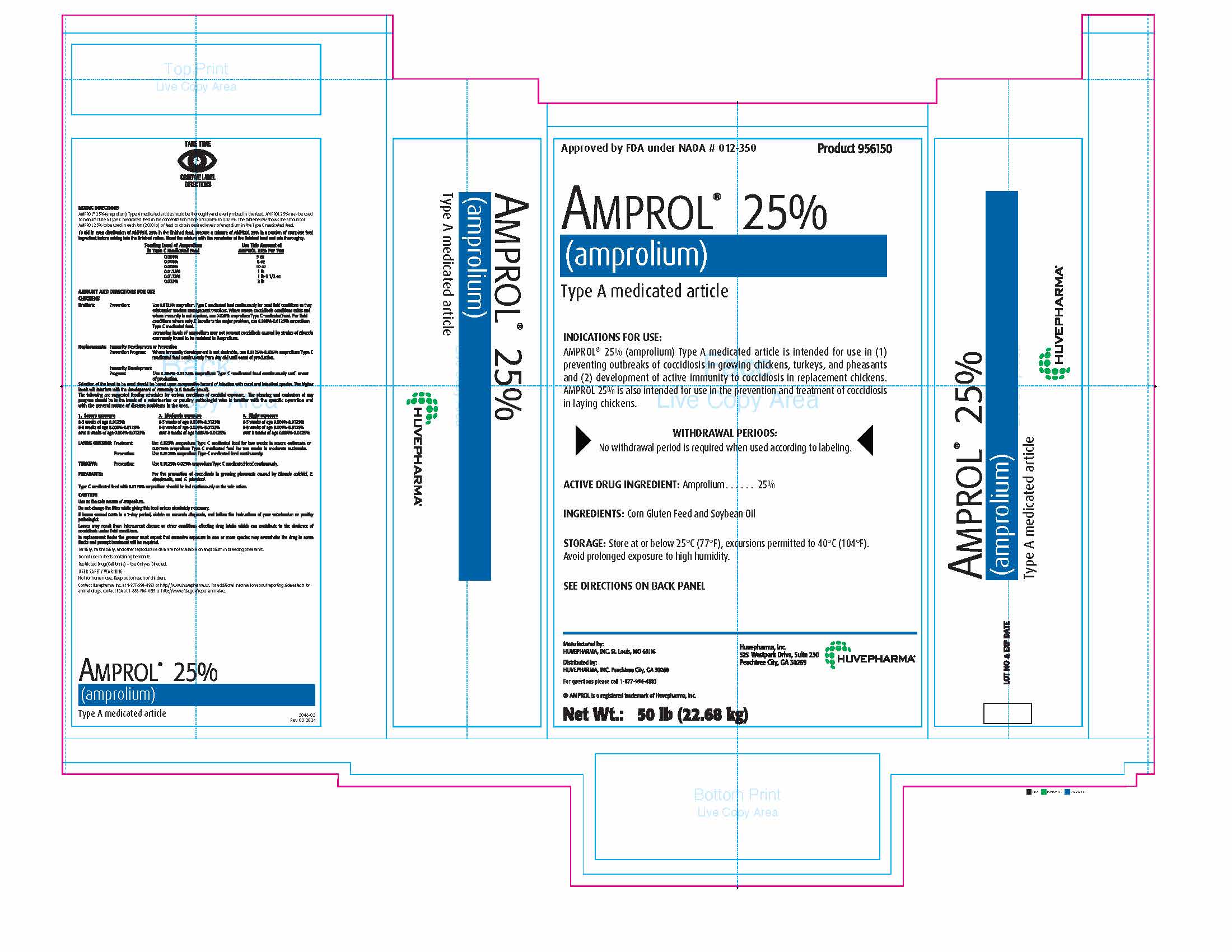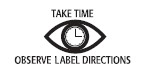 DRUG LABEL: Amprol 25
NDC: 23243-9561 | Form: POWDER
Manufacturer: Huvepharma, Inc.
Category: animal | Type: OTC TYPE A MEDICATED ARTICLE ANIMAL DRUG LABEL
Date: 20251013

ACTIVE INGREDIENTS: AMPROLIUM 250 g/1 kg
INACTIVE INGREDIENTS: CORN GLUTEN AMINO ACIDS; SOYBEAN OIL

Approved by FDA under NADA # 012-350 Product 956150

AMPROL® 25%
(amprolium)
Type A Medicated Article

INDICATIONS FOR USE:

AMPROL® 25% (amprolium) Type A medicated article is intended for use in (1)
preventing outbreaks of coccidiosis in growing chickens, turkeys, and pheasants
and (2) development of active immunity to coccidiosis in replacement chickens.
AMPROL 25% is also intended for use in the prevention and treatment of
coccidiosis in laying chickens.

RESIDUE WARNING

WITHDRAWAL PERIODS:
No withdrawal period is required when used according to labeling.

ACTIVE DRUG INGREDIENT: Amprolium. . . . . . 25%

INACTIVE INGREDIENT

INGREDIENTS: Corn Gluten Feed and Soybean Oil

STORAGE AND HANDLING

STORAGE: Store at or below 25°C (77°F), excursions permitted to 40°C (104°F).
Avoid prolonged exposure to high humidity.

SEE DIRECTIONS ON BACK PANEL

Manufactured by:
HUVEPHARMA, INC. St. Louis, MO 63116

Huvepharma, Inc.
525 Westpark Drive, Suite 230
Peachtree City, GA 30269

Distributed by:
HUVEPHARMA, INC. Peachtree City, GA 30269

For questions please call 1-877-994-4883

®AMPROL is a registered trademark of Huvepharma, Inc.

Net Wt.: 50 lb (22.68 kg)

DOSAGE AND ADMINISTRATION

MIXING DIRECTIONS
AMPROL® 25% (amprolium) Type A medicated article should be thoroughly and evenly mixed in the feed. AMPROL 25% may be used
to manufacture a Type C medicated feed in the concentration range of 0.004% to 0.025%. The table below shows the amount of
AMPROL 25% to be used in each ton (2000 lb) of feed to obtain desired levels of amprolium in the Type C medicated feed.

To aid in even distribution of AMPROL 25% in the finished feed, prepare a mixture of AMPROL 25% in a portion of complete feed
ingredient before mixing into the finished ration. Blend the mixture with the remainder of the finished feed and mix thoroughly.

Feeding level of Amprolium; in Type C Medicated Feed | Use This Amount of; AMPROL 25% Per Ton
0.004% | 5 oz
0.006% | 8 oz
0.008% | 10 oz
0.0125% | 1 lb
0.0175% | 1 lb 6 ½ oz
0.025% | 2 lb

AMOUNT AND DIRECTIONS FOR USE CHICKENS

Broilers: | Prevention: | Use 0.0125% amprolium Type C medicated feed continuously for most field conditions as they exist under modern management practices. Where severe coccidiosis conditions exists and where immunity is not required, use 0.025% amprolium Type C medicated feed. For field conditions where only E. tenella is the major problem, use 0.008%-0.0125% amprolium Type C medicated feed.
 |  | Increasing levels of amprolium may not prevent coccidiosis caused by strains of Eimeria; commonly found to be resistant to Amprolium.
Replacements: | Immunity Development or Prevention
 | Prevention Program: | Where immunity development is not desirable, use 0.0125%-0.025% amprolium Type C; medicated feed continuously from day old until onset of production.
 | Immunity Development
 | Program: | Use 0.004%-0.0125% amprolium Type C medicated feed continuously until onset of production.

Selection of the level to be used should be based upon comparative hazard of infection with cecal and intestinal species. The higher
levels will interfere with the development of immunity to E. tenella (cecal).
The following are suggested feeding schedules for various conditions of coccidial exposure. The planning and evaluation of any
program should be in the hands of a veterinarian or poultry pathologist who is familiar with the specific operation and with the
general nature of disease problems in the area.

1. Severe exposure | 2. Moderate exposure | 3. Slight exposure
0-5 weeks of age 0.0125% | 0-5 weeks of age 0.008%-0.0125% | 0-5 weeks of age 0.004%-0.0125%
5-8 weeks of age 0.008%-0.0125% | 5-8 weeks of age 0.006%-0.0125% | 5-8 weeks of age 0.004%-0.0125%
over 8 weeks of age 0.004%-0.0125% | over 8 weeks of age 0.004%-0.0125% | over 8 weeks of age 0.004%-0.0125%

LAYING CHICKENS: | Treatment: | Use 0.025% amprolium Type C medicated feed for two weeks in severe outbreaks or; 0.0125% amprolium Type C medicated feed for two weeks in moderate outbreaks.
 | Prevention: | Use 0.0125% amprolium Type C medicated feed continuously.
TURKEYS: | Prevention: | Use 0.0125%-0.025% amprolium Type C medicated feed continuously.
PHEASANTS: |  | For the prevention of coccidiosis in growing pheasants caused by Eimeria colchici, E. duodenalis,; and E. phasiani.

Type C medicated feed with 0.0175% amprolium should be fed continuously as the sole ration.

GENERAL PRECAUTIONS

CAUTION

Use as the sole source of amprolium.

Do not change the litter while giving this feed unless absolutely necessary.

If losses exceed 0.5% in a 2-day period, obtain an accurate diagnosis, and follow the instructions of your veterinarian or poultry pathologist.

Losses may result from intercurrent disease or other conditions affecting drug intake which can contribute to the virulence of coccidiosis under field conditions.

In replacement flocks the grower must expect that excessive exposure to one or more species may overwhelm the drug in some flocks and prompt treatment will be required.

Fertility, hatchability and other reproductive data are not available on amprolium in breeding pheasants.

Do not use in feeds containing bentonite.

Restricted Drug (California) - Use Only as Directed.

USER SAFETY WARNING
Not for human use. Keep out of reach of children.
Contact Huvepharma Inc. at 1-877-994-4883 or http://www.huvepharma.us. For additional information about reporting side effects for
animal drugs, contact FDA at 1-888-FDA-VETS or http://www.fda.gov/reportanimalae.